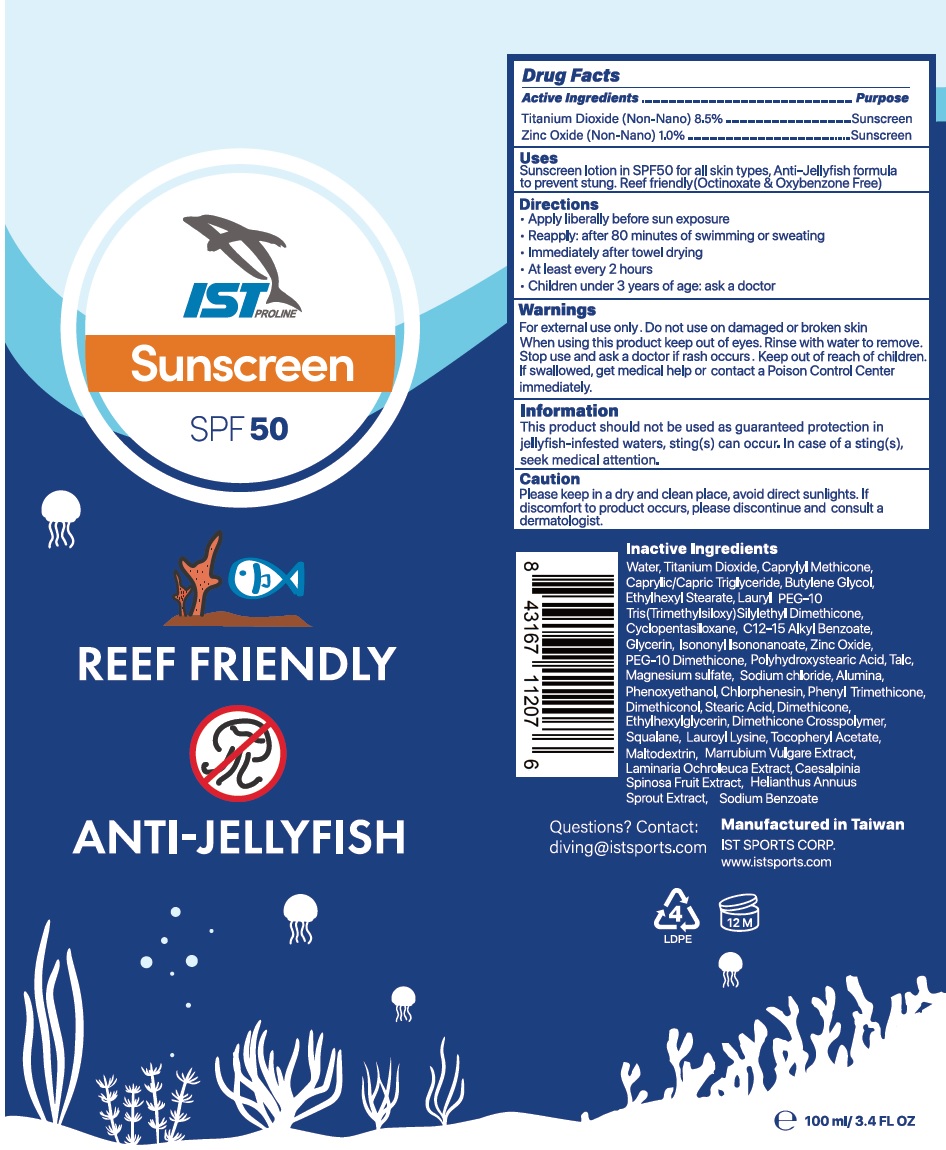 DRUG LABEL: IST Sunscreen SPF 50
NDC: 82589-000 | Form: CREAM
Manufacturer: IST DIVING SYSTEM, INC
Category: otc | Type: HUMAN OTC DRUG LABEL
Date: 20231226

ACTIVE INGREDIENTS: TITANIUM DIOXIDE 85 mg/1 mL; ZINC OXIDE 10 mg/1 mL
INACTIVE INGREDIENTS: CHLORPHENESIN; PHENYL TRIMETHICONE; STEARIC ACID; DIMETHICONE; ETHYLHEXYLGLYCERIN; SQUALANE; LAUROYL LYSINE; .ALPHA.-TOCOPHEROL ACETATE; MALTODEXTRIN; HOREHOUND; LAMINARIA OCHROLEUCA; HELIANTHUS ANNUUS SPROUT; SODIUM BENZOATE; CAPRYLYL TRISILOXANE; WATER; MEDIUM-CHAIN TRIGLYCERIDES; BUTYLENE GLYCOL; ETHYLHEXYL STEARATE; CYCLOMETHICONE 5; ALKYL (C12-15) BENZOATE; GLYCERIN; ISONONYL ISONONANOATE; TALC; MAGNESIUM SULFATE, UNSPECIFIED FORM; SODIUM CHLORIDE; ALUMINUM OXIDE; PHENOXYETHANOL

IST Sunscreen SPF 50

Active Ingredients

Titanium Dioxide (Non-Nano) 8.5%

Zinc Oxide (Non-Nano) 1.0%

Purpose

Sunscreen

Uses

Sunscreen lotion in SPF50 for all skin types, Anti-Jellyfish formula to prevent stung. Reef friendly(Octinoxate & Oxybenzone Free)

Directions

- Apply liberally before sun exposure
- Reapply: after 80 minutes of swimming or sweating
- Immediately after towel drying
- At least every 2 hours
- Children under 3 years of age: ask a doctor

Warnings

For external use only.

Do not use

on damaged or broken skin

When using this product

keep out of eyes. Rinse with water to remove.

Stop use and ask a doctor

ir rash occurs.

Keep out of reach of children.

If swallowed, get medical help or contact a Poison Control Center immediately.

Information

This product should not be used as guaranteed protection in jellyfish-infested waters, sting(s) can occur. In case of a sting(s), seek medical attention.

Caution

Please keep in a dry and clean place, avoid direct sunlights. If discomfort to product occurs, please discontinue and consult a dermatologist.

Inactive Ingredients

Water, Titanium Dioxide, Caprylyl Methicone, Caprylic/Capric Triglyceride, Butylene Glycol, Ethylhexyl Stearate, Lauryl PEG-10 Tris(Trimethylsiloxy) Silylethyl Dimethicone, Cyclopentasiloxane, C12-15 Alkyl Benzoate, Glycerin, Isononyl isononanoate, Zinc Oxide, PEG-10 Dimethicone, Polyhydroxystearic Acid, Talc, Magnesium sulfate, Sodium chloride, Alumina, Phenoxyethanol, Chlorphenesin, Phenyl Trimethicone, Dimethiconol, Stearic Acid, Dimethicone, Ethylhexylglycerin, Dimethicone Crosspolymer, Squalane, Lauroyl Lysine, Tocopheryl Acetate, Maltodextrin, Marrubium Vulgare Extract, Laminaria Ochroleuca Extract, Caesalpinia Spinosa Fruit Extract, Helianthus Annuus Sprout Extract, Sodium Benzoate

Questions?

Contact: diving@istsports.com